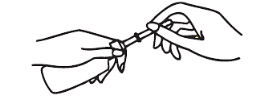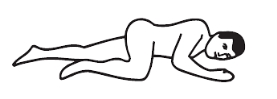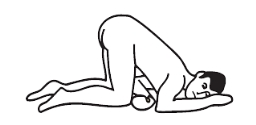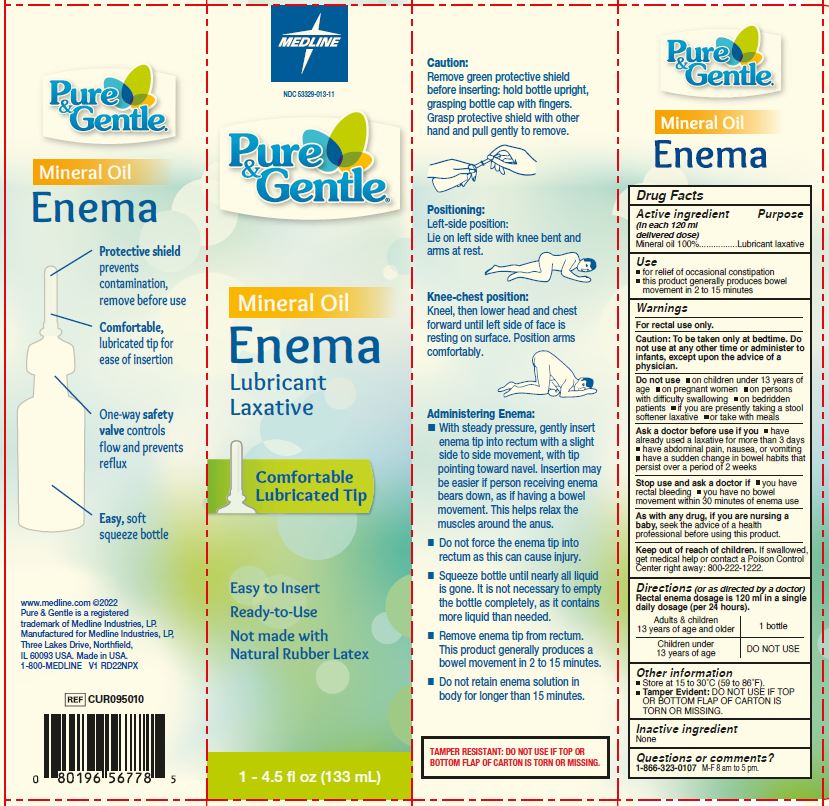 DRUG LABEL: Pure and Gentle
NDC: 53329-013 | Form: ENEMA
Manufacturer: Medline Industries, LP
Category: otc | Type: HUMAN OTC DRUG LABEL
Date: 20241126

ACTIVE INGREDIENTS: MINERAL OIL 100 g/100 mL

013 Pure & Gentle Mineral Oil Enema

Active ingredient (in each 120 mL delivered dose)

Mineral oil 100% w/v

Purpose

Lubricant laxative

Uses

- for relief of occasional constipation
- this product generally produces bowel movement in 2 to 15 minutes

Warnings

For rectal use only

Caution: to be taken only at bedtime. Do not use at any other time or administer to infants, except upon the advice of a physician.

Do not use

- on children under 13 years of age
- on pregnant women
- on persons with difficulty swallowing
- on bedridden patients
- if you are presently taking a stool softener laxative
- or take with meals

Ask a doctor before use if you

- have already used a laxative for more than 3 days
- have abdominal pain, nausea or vomiting
- have a sudden change in bowel habits that persists over a period of 2 weeks

Stop use and ask a doctor if

- you have rectal bleeding
- you have no bowel movement within 30 minutes of enema use

As with any drug, if you are nursing a baby,

seek the advice of a health professional before using this product.

Keep out of reach of children.

If swallowed, get medical help or contact a Poison Control Center right away. (1-800-222-1222)

Directions (or as directed by a doctor)

Rectal enema dosage is 120 mL in a single daily dosage (per 24 hours)

adults & children; 13 years and over | 1 bottle
children under 13 years of age | DO NOT USE

Caution:

Remove green protective shield before inserting: hold bottle upright, grasping bottle cap with fingers. Grasp protective shield with other hand and pull gently to remove

Positioning:

Left-side position: Lie on left side with knee bent and arms at rest.

Knee-chest position: Kneel, then lower head and chest forward until left side of face is resting on surface. Position arms comfortably.

Administering enema:

- With steady pressure, gently insert enema tip into rectum with a slight side-to-side movement, with tip pointing toward navel. Insertion may be easier if person receiving enema bears down, as if having a bowel movement. This helps relax the muscles around the anus.
- Do not force the enema tip into rectum as this can cause injury.
- Squeeze bottle until nearly all liquid is gone. It is not necessary to empty the bottle completely, as it contains more liquid than needed.
- Remove enema tip from rectum. This product generally produces a bowel movement in 2 to 15 minutes.
- Do not retain enema solution in body for longer than 15 minutes.

Other Information

- store at room temperature 15-30°C (59-86°F)
- Tamper Evident: DO NOT USE IF TOP OR BOTTOM FLAP OF CARTON IS TORN OR MISSING.

Inactive ingredient

none

Questions or comments?

1-866-323-0107 M-F 8 am to 5 pm

Manufacturing Information

Manufactured for: Medline Industries, LP

Three Lakes Drive, Northfield, IL 60093

Made in USA

www.medline.com

1-800-MEDLINE (633-5463)

REF: CUR095010

V1 RD22NPX